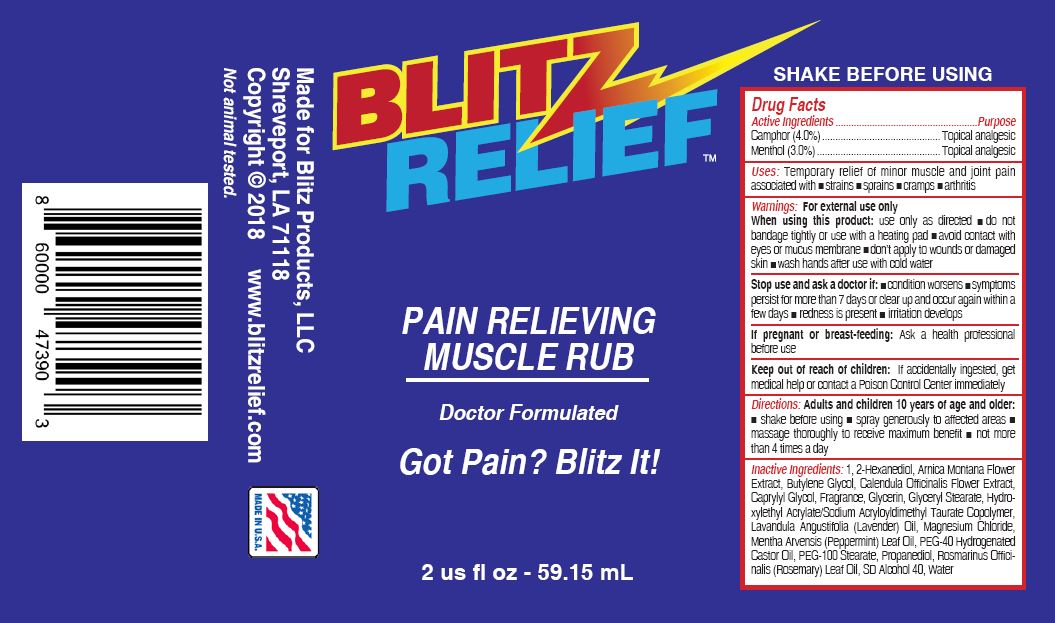 DRUG LABEL: BLITZ RELIEF
NDC: 72676-101 | Form: SPRAY
Manufacturer: BLITZ PRODUCTS LLC
Category: otc | Type: HUMAN OTC DRUG LABEL
Date: 20220120

ACTIVE INGREDIENTS: MENTHOL 3 g/100 mL; CAMPHOR (SYNTHETIC) 4 g/100 mL
INACTIVE INGREDIENTS: 1,2-HEXANEDIOL; ARNICA MONTANA FLOWER; BUTYLENE GLYCOL; CALENDULA OFFICINALIS FLOWER; CAPRYLYL GLYCOL; GLYCERIN; GLYCERYL MONOSTEARATE; HYDROXYETHYL ACRYLATE/SODIUM ACRYLOYLDIMETHYL TAURATE COPOLYMER (45000 MPA.S AT 1%); LAVENDER OIL; MAGNESIUM CHLORIDE; PEPPERMINT OIL; POLYOXYL 40 HYDROGENATED CASTOR OIL; PEG-100 STEARATE; PROPANEDIOL; ROSEMARY OIL; ALCOHOL; WATER

BLITZ RELIEF PAIN RELIEVING MUSCLE RUB (72676-101)

ACTIVE INGREDIENTS

CAMPHOR (4.0%)

MENTHOL (3.0%)

PURPOSE

TOPICAL ANALGESIC

USES

Temporary relief of minor muscle and joint pain associated with

- strains
- sprains
- cramps
- arthritis

WARNINGS

For external use only

When using this product: use only as directed

- do not bandage tightly or use with a heating pad
- avoid contact with eyes or mucus membrane
- don’t apply to wounds or damaged skin
- wash hands after use with cold water

Stop use and ask a doctor if:

- condition worsens
- symptoms persist for more than 7 days or clear up and occur again within a few days
- redness is present
- irritation develops

If pregnant or breast-feeding: Ask a health professional before use

Keep out of reach of children: If accidentally ingested, get medical help or contact a Poison Control Center immediately

DIRECTIONS

Adults and children 10 years of age and older:

- shake before using
- spray generously to affected areas
- massage thoroughly to receive maximum benefit
- not more than 4 times a day

INACTIVE INGREDIENTS

1, 2-Hexanediol, Arnica Montana Flower Extract, Butylene Glycol, Calendula Officinalis Flower Extract, Caprylyl Glycol, Fragrance, Glycerin, Glyceryl Stearate, Hydroxylethyl Acrylate/Sodium Acryloyldimethyl Taurate Copolymer, Lavandula Angustifolia (Lavender) Oil, Magnesium Chloride, Mentha Arvensis (Peppermint) Leaf Oil, PEG-40 Hydrogenated Castor Oil, PEG-100 Stearate, Propanediol, Rosmarinus Officinalis (Rosemary) Leaf Oil, SD Alcohol 40, Water